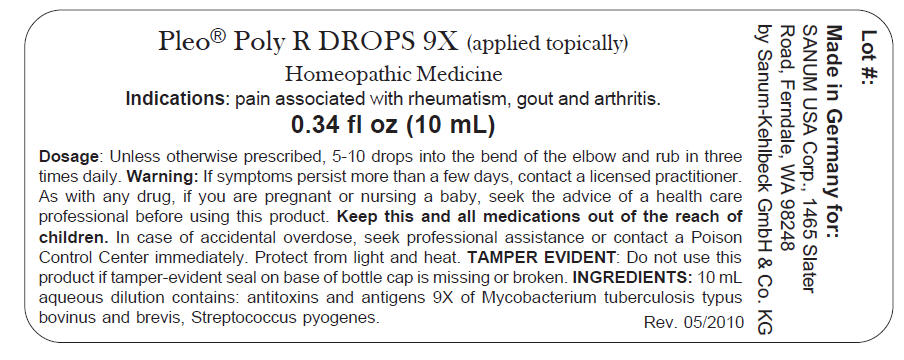 DRUG LABEL: Pleo Poly R
NDC: 60681-2809 | Form: LIQUID
Manufacturer: Sanum Kehlbeck GmbH & Co. KG
Category: homeopathic | Type: HUMAN OTC DRUG LABEL
Date: 20101008

ACTIVE INGREDIENTS: mycobacterium bovis immunoserum rabbit 9 [hp_X]/10 mL; mycobacterium microti immunoserum rabbit 9 [hp_X]/10 mL; streptococcus pyogenes immunoserum rabbit 9 [hp_X]/10 mL
INACTIVE INGREDIENTS: water

Pleo® Poly R
DROPS 9X

PURPOSE

Homeopathic Medicine

0.34 fl oz
(10 mL)

Indications

pain associated with rheumatism, gout and arthritis.

DOSAGE

Unless otherwise prescribed, apply 5-10 drops into the bend of the elbow and rub in three times daily.

WARNING

ASK DOCTOR

If symptoms persist more than a few days, contact a licensed practitioner.

PREGNANCY OR BREAST FEEDING

As with any drug, if you are pregnant or nursing a baby, seek the advice of a health care professional before using this product.

KEEP OUT OF REACH OF CHILDREN

Keep this and all other medications out of the reach of children. In case of accidental ingestion, seek professional assistance or contact a Poison Control Center immediately.

WHEN USING

Protect from light and heat.

INGREDIENTS

10 mL aqueous dilution contains: antitoxins and antigens 9X of Mycobacterium tuberculosis typus bovinus and brevis, Streptococcus pyogenes.

Inactive Ingredient water

Tamper Evident

Do not use this product if tamper-evident strip on base of bottle cap is missing or broken.

Made in Germany

Distributed by:
SANUM USA Corp.
1465 Slater Road
Ferndale, WA 98248

Manufactured by:
Sanum-Kehlbeck
GmbH & Co. KG
Hoya, Germany

Rev. 05/2010

PRINCIPAL DISPLAY PANEL - 10 mL Bottle Label

Pleo® Poly R DROPS 9X (applied topically)

Homeopathic Medicine
Indications: pain associated with rheumatism, gout and arthritis.
0.34 fl oz (10 mL)

Dosage: Unless otherwise prescribed, 5-10 drops into the bend of the elbow and rub in three
times daily. Warning: If symptoms persist more than a few days, contact a licensed practitioner.
As with any drug, if you are pregnant or nursing a baby, seek the advice of a health care
professional before using this product. Keep this and all medications out of the reach of
children. In case of accidental overdose, seek professional assistance or contact a Poison
Control Center immediately. Protect from light and heat. TAMPER EVIDENT: Do not use this
product if tamper-evident seal on base of bottle cap is missing or broken. INGREDIENTS: 10 mL
aqueous dilution contains: antitoxins and antigens 9X of Mycobacterium tuberculosis typus
bovinus and brevis, Streptococcus pyogenes.
Rev. 05/2010